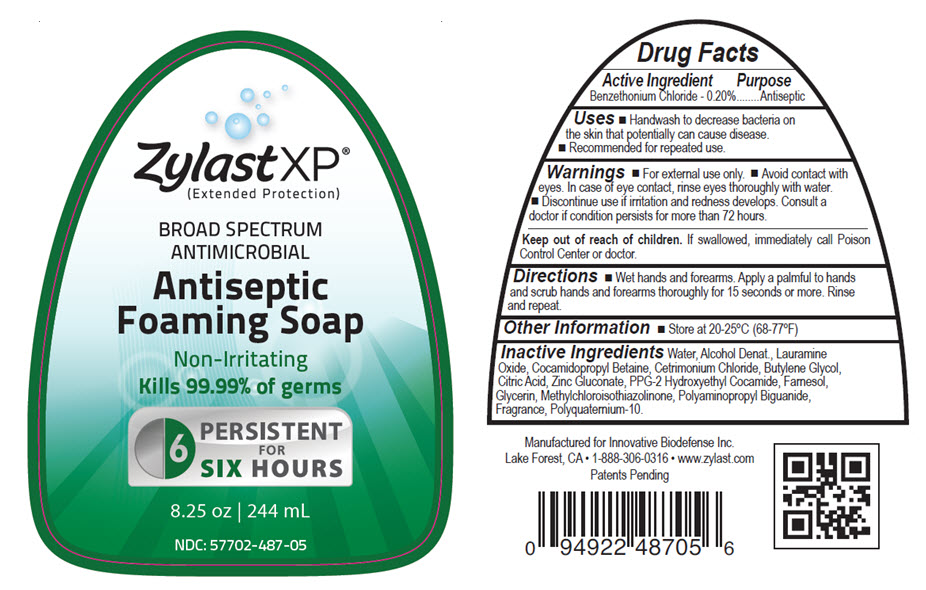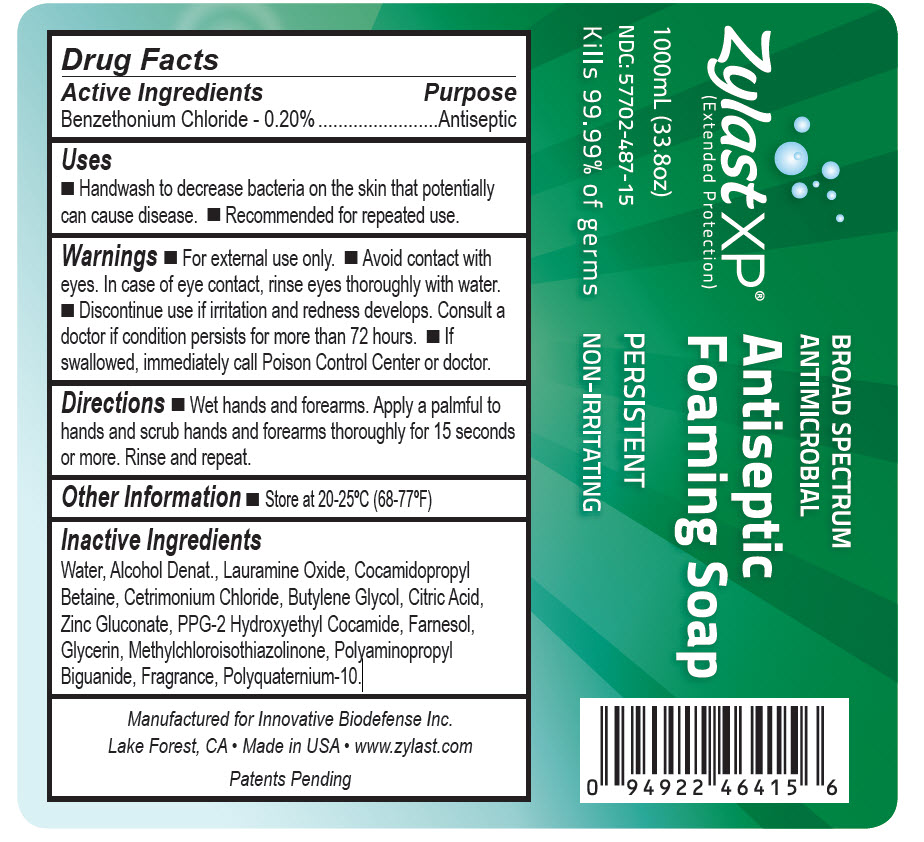 DRUG LABEL: Zylast XP Antiseptic Foaming
NDC: 57702-487 | Form: SOAP
Manufacturer: Bocchi Laboratories Inc.
Category: otc | Type: HUMAN OTC DRUG LABEL
Date: 20140331

ACTIVE INGREDIENTS: BENZETHONIUM CHLORIDE 2 mg/1 mL
INACTIVE INGREDIENTS: WATER; LAURAMINE OXIDE; COCAMIDOPROPYL BETAINE; CETRIMONIUM CHLORIDE; BUTYLENE GLYCOL; CITRIC ACID MONOHYDRATE; ZINC GLUCONATE; PPG-2 HYDROXYETHYL COCAMIDE; FARNESOL; GLYCERIN; METHYLCHLOROISOTHIAZOLINONE; POLIHEXANIDE

Zylast Antiseptic Foaming Soap
Drug Facts

Active Ingredients

Benzethonium Chloride - 0.20%

Purpose

Antiseptic

Uses

- Handwash to decrease bacteria on the skin that potentially can cause disease.
- Recommended for repeated use.

Warnings

- For external use only.
- Avoid contact with eyes. In case of eye contact, rinse thoroughly with water.
- Discontinue use if irritation and redness develops. Consult a doctor if condition persists for more than 72 hours.
- If swallowed, immediately call Poison Control Center or doctor.

Keep out of reach of children.

If swallowed, immediately call Poison Control Center or doctor.

Directions

- Wet hands and forearms. Apply a palmful to hands and scrub hands and forearms thoroughly for 15 seconds or more. Rinse and repeat.

Other Inforamtion

- Store at 20-25°C (68-77°F)

Inactive Ingredients

Water, Alcohol Denat., Lauramine Oxide, Cocamidopropyl Betaine, Cetrimonium Chloride, Butylene Glycol, Citric Acid, Zinc Gluconate, PPG-2 Hydroxyethyl Cocamide, Farnesol, Glycerin, Methylchloroisothiazolinone, Polyaminopropyl Biguanide, Fragrance, Polyquaternium-10.

Active Ingredients

Benzethonium Chloride - 0.20%

Purpose

Antiseptic

Uses

- Handwash to decrease bacteria on the skin that potentially can cause disease.
- Recommended for repeated use.

Warnings

- For external use only.
- Avoid contact with eyes. In case of eye contact, rinse thoroughly with water.
- Discontinue use if irritation and redness develops. Consult a doctor if condition persists for more than 72 hours.
- If swallowed, immediately call Poison Control Center or doctor.

Directions

- Wet hands and forearms. Apply a palmful to hands and scrub hands and forearms thoroughly for 15 seconds or more. Rinse and repeat.

Other Information

- Store at 20-25°C (68-77°F)

Inactive ingredients

Water, Alcohol Denat., Lauramine Oxide, Cocamidopropyl Betaine, Cetrimonium Chloride, Butylene Glycol, Citric Acid, Zinc Gluconate, PPG-2 Hydroxyethyl Cocamide, Farnesol, Glycerin, Methylchloroisothiazolinone, Polyaminopropyl Biguanide, Fragrance, Polyquaternium-10.

Package/Label Principal Display Panel

NDC 57702-487-05
Zylast XP
Extended Protection
Broad Spectrum
Antimicrobial
Antiseptic
Foaming Soap
8.25 oz 244mL

Package/Label Principal Display Panel

NDC 57702-487-15
Zylast XP
Extended Protection
Broad Spectrum
Antimicrobial
Antiseptic
Foaming Soap
1000mL (33.8oz)